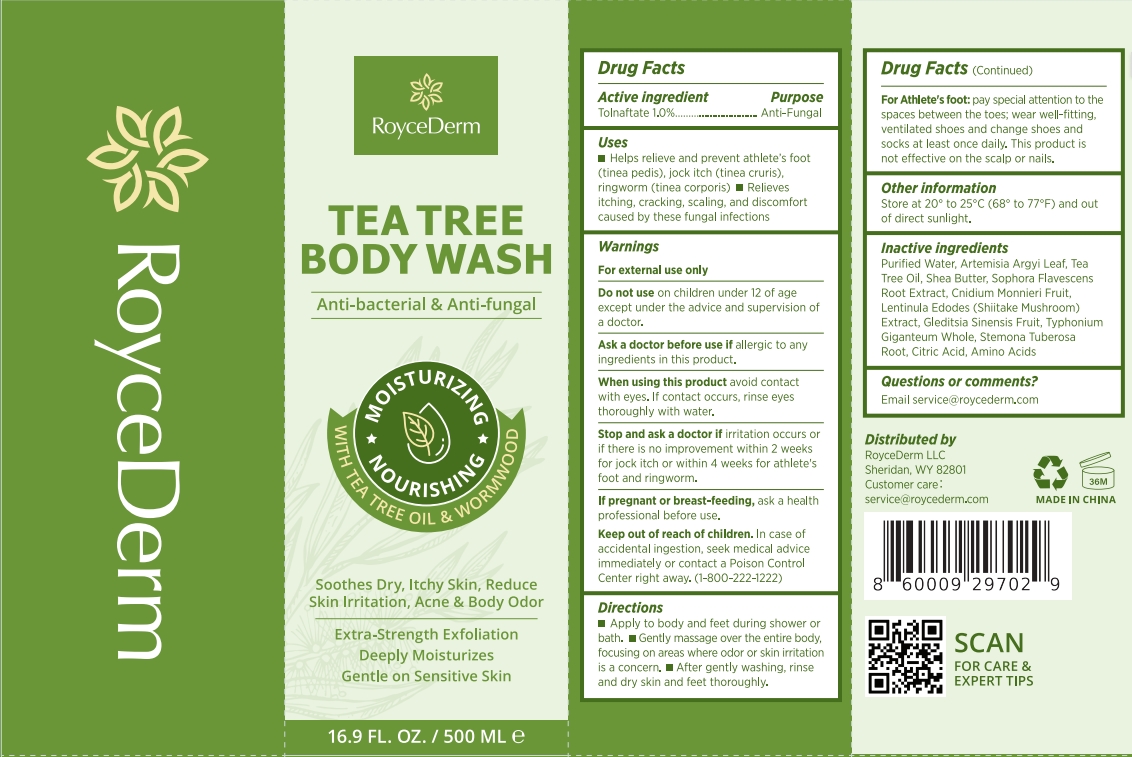 DRUG LABEL: RoyceDerm Tea Tree Body Wash
NDC: 85424-002 | Form: GEL
Manufacturer: RoyceDerm LLC
Category: otc | Type: HUMAN OTC DRUG LABEL
Date: 20251119

ACTIVE INGREDIENTS: TOLNAFTATE 1 g/100 g
INACTIVE INGREDIENTS: GLEDITSIA SINENSIS FRUIT; CITRIC ACID; AMINO ACIDS; LENTINULA EDODES MYCELIUM; WATER; CNIDIUM MONNIERI FRUIT; ARTEMISIA ARGYI LEAF; SOPHORA FLAVESCENS ROOT; SAUROMATUM GIGANTEUM WHOLE; SHEA BUTTER; TEA TREE OIL; STEMONA TUBEROSA ROOT

Initial Drug Listing - RoyceDerm Tea Tree Body Wash

ACTIVE INGREDIENT

Tolnaftate 1.0%

PURPOSE

Anti-Fungal

INDICATIONS AND USAGE

- Helps relieve and prevent athlete's foot(tinea pedis), jock itch (tinea cruris),ringworm(tinea corporis)
- Relieves itching, cracking, scaling, and discomfort caused by these fungal infections

WARNINGS

For external use only

DO NOT USE

on children under 12 of age except under the advice and supervision of a doctor.

Ask a doctor before use if allergic to anyingredients in this product.

WHEN USING

avoid contact with eyes. lf contact occurs, rinse eyes thoroughly with water.

STOP USE

Stop and ask a doctor if irritation occurs or if there is no improvement within 2 weeks for jock itch or within 4 weeks for athlete's foot and ringworm.

PREGNANCY OR BREAST FEEDING

ask a health professional before use

KEEP OUT OF REACH OF CHILDREN

In case of accidental ingestion, seek medical advice immediately or contact a Poison Control Center right away.(1-800-222-1222)

DOSAGE AND ADMINISTRATION

- Apply to body and feet during shower or bath.
- Gently massage over the entire body,focusing on areas where odor or skin irritation is a concern.
- After gently washing, rinseand dry skin and feet thoroughly.
- For Athllete's foot: pay special attention to the spaces between the toes; wear well-fitting,ventilated shoes and change shoes and socks at least once daily. This product is not effective on the scalp or nails.

OTHER SAFETY INFORMATION

Store at 20° to 25°C(68° to 77°F) and out of direct sunlight.

INACTIVE INGREDIENT

Purified Water, Artemisia Argyi Leaf, TeaTree Oil, Shea Butter, Sophora Flavescens Root Extract, Cnidium Monnieri Fruit,Lentinula Edodes (Shiitake Mushroom)Extract, Gleditsia Sinensis Fruit, Typhonium Giganteum Whole, Stemona Tuberosa Root, Citric Acid, Amino Acids

QUESTIONS

Email service@roycederm.com